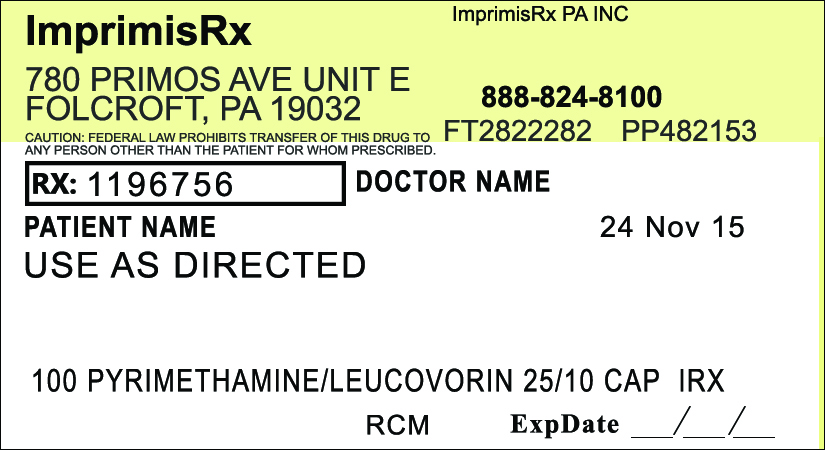 DRUG LABEL: Pyrimethamine Leucovorin
NDC: 70271-427 | Form: CAPSULE
Manufacturer: ImprimisRx PA, Inc. d/b/a ImprimisRx
Category: prescription | Type: HUMAN PRESCRIPTION DRUG LABEL
Date: 20151127

ACTIVE INGREDIENTS: PYRIMETHAMINE 25 mg/1 1; LEUCOVORIN CALCIUM 10 mg/1 1
INACTIVE INGREDIENTS: CELLULOSE, MICROCRYSTALLINE 85 mg/1 1

Pyrimethamine Leucovorin (25mg-10mg)